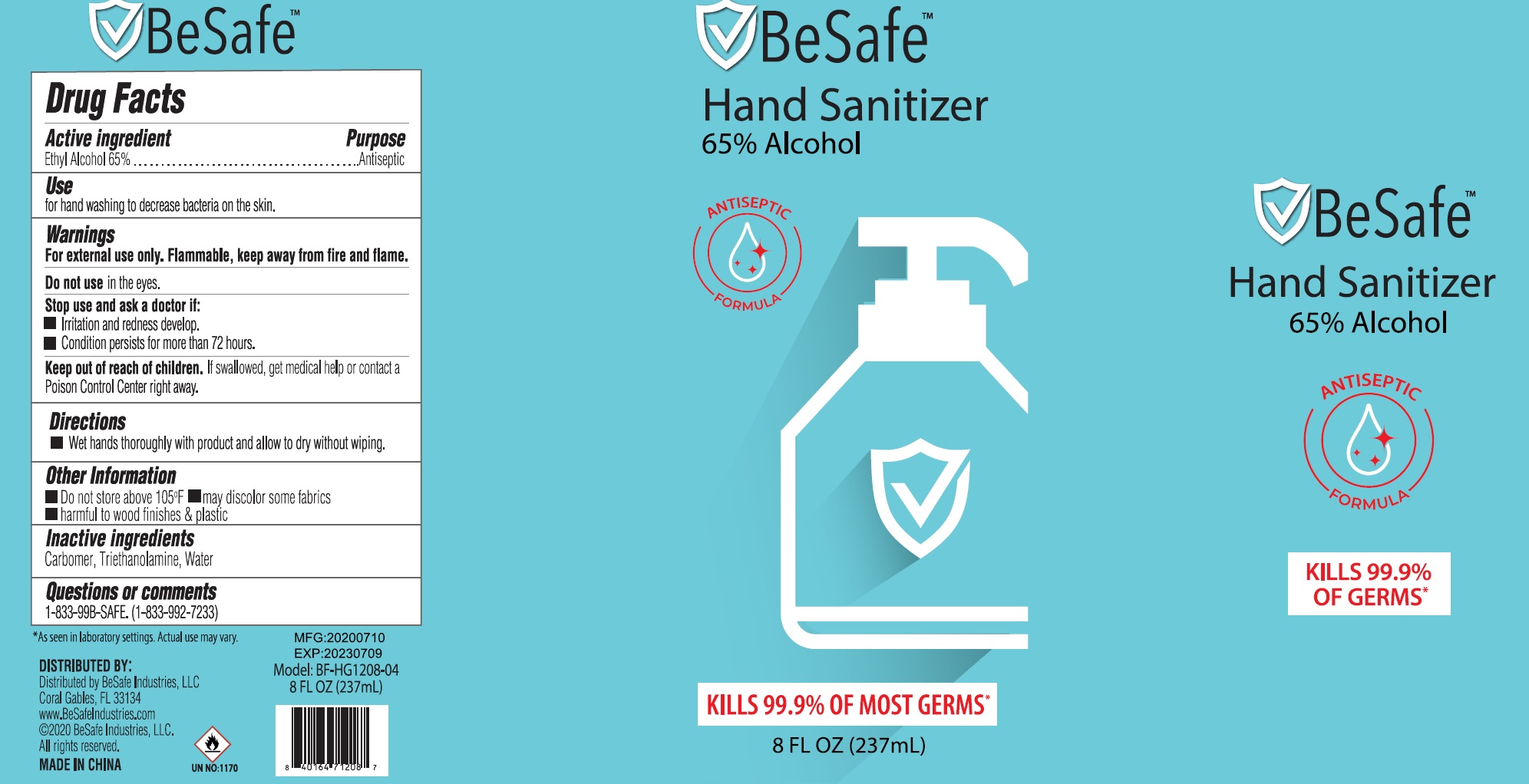 DRUG LABEL: Hand Sanitizer
NDC: 77693-010 | Form: GEL
Manufacturer: BeSafe Industries LLC
Category: otc | Type: HUMAN OTC DRUG LABEL
Date: 20231026

ACTIVE INGREDIENTS: ALCOHOL 0.65 mL/1 mL
INACTIVE INGREDIENTS: CARBOMER HOMOPOLYMER, UNSPECIFIED TYPE; TROLAMINE; WATER

Hand Sanitizer

Active ingredients

Ethyl Alcohol 65%

Purpose

Antiseptic

Use

for hand washing to decrease bacteria on the skin.

Warnings

For external use only. Flammable, keep away from fire and flame.

Do not use

in the eyes.

Stop use and ask a doctor if:

- Irritation and redness develop.
- Condition persists for more than 72 hours.

Keep out of reach of children.

If swallowed, get medical help or contact a Poison Control Center right away.

Directions

- Wet hands thoroughly with product and allow to dry without wiping.

Other Information

- Do not store above 105°F
- may discolor some fabrics
- harmful to wood finishes & plastic

Inactive ingredients

Carbomer, Triethanolamine, Water

Questions or comments

1-833-99B-SAFE. (1-833-992-7233)